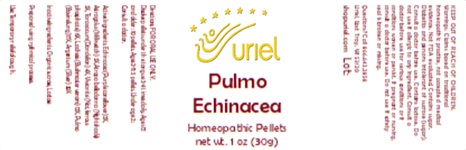 DRUG LABEL: Pulmo Echinacea
NDC: 48951-8086 | Form: PELLET
Manufacturer: Uriel Pharmacy Inc.
Category: homeopathic | Type: HUMAN OTC DRUG LABEL
Date: 20260116

ACTIVE INGREDIENTS: ECHINACEA ANGUSTIFOLIA 2 [hp_X]/1 1; ASTRAGALUS PROPINQUUS ROOT 3 [hp_X]/1 1; ATROPA BELLADONNA 3 [hp_X]/1 1; TARAXACUM PALUSTRE ROOT 4 [hp_X]/1 1; FERROSOFERRIC PHOSPHATE 6 [hp_X]/1 1; LACHESIS MUTA VENOM 12 [hp_X]/1 1; SUS SCROFA LUNG 17 [hp_X]/1 1; SILVER 30 [hp_X]/1 1
INACTIVE INGREDIENTS: SUCROSE; LACTOSE

Pulmo Echinacea

INDICATIONS AND USAGE

Directions: FOR ORAL USE ONLY.

DOSAGE AND ADMINISTRATION

Dissolve pellets under the tongue 3-4 times daily. Ages 12 and older: 10 pellets. Ages 2-11: 5 pellets. Under age 2: Consult a doctor.

ACTIVE INGREDIENT

Active Ingredients: Echinacea (Purple coneflower) 2X, Astragalus (Milk vetch) 3X, Atropa belladonna (Nightshade) 3X, Taraxacum (Dandelion) 4X, Vivianite (Nat. ferrous phosphate) 6X, Lachesis (Bushmaster venom) 12X, Pulmo (Bovine lung)17X, Argentum (Silver) 30X

PURPOSE

Use: Temporary relief of cough.

KEEP OUT OF REACH OF CHILDREN.

Inactive Ingredients: Organic sucrose, Lactose

Prepared using rythmical processes.

WARNINGS

Warnings: Claims based on traditional homeopathic practice, not accepted medical evidence. Not FDA evaluated. Contains sugar. Diabetics and persons intolerant of sucrose (sugar): Consult a doctor before use. Do not use if allergic to any ingredient. Contains traces of lactose. Consult a doctor before use for serious conditions or if conditions worsen or persist. If pregnant or nursing, consult a doctor before use. Do not use if safety seal is broken or missing.

Questions? Call 866.642.2858
Uriel, East Troy, WI 53120
shopuriel.com Lot: